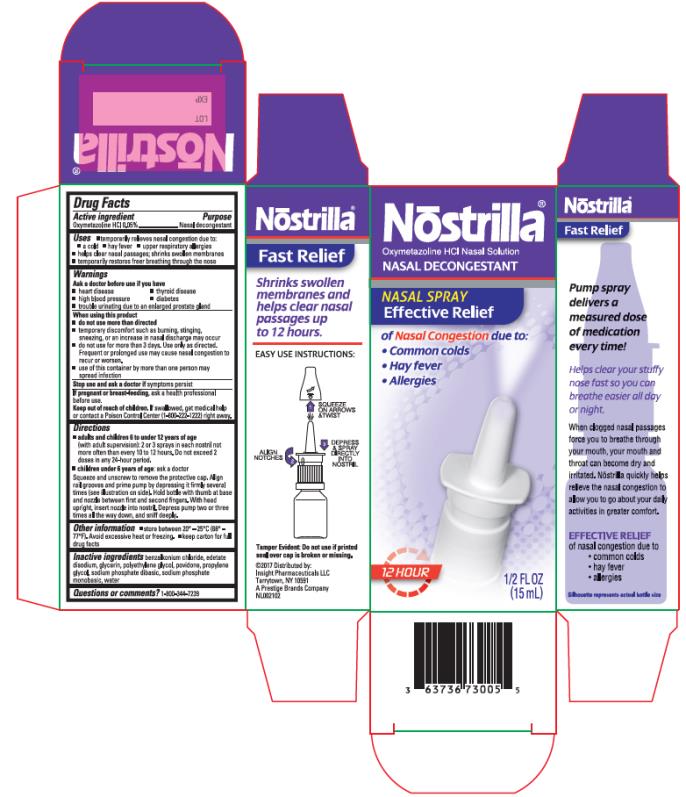 DRUG LABEL: Nostrilla
NDC: 63736-730 | Form: SPRAY, METERED
Manufacturer: Insight Pharmaceuticals LLC
Category: otc | Type: HUMAN OTC DRUG LABEL
Date: 20241025

ACTIVE INGREDIENTS: OXYMETAZOLINE HYDROCHLORIDE 0.05 mg/100 mL
INACTIVE INGREDIENTS: BENZALKONIUM CHLORIDE; EDETATE DISODIUM; GLYCERIN; POLYETHYLENE GLYCOL, UNSPECIFIED; POVIDONE; PROPYLENE GLYCOL; SODIUM PHOSPHATE, DIBASIC, ANHYDROUS; SODIUM PHOSPHATE, MONOBASIC, ANHYDROUS; WATER

Nostrilla

Drug Facts

Active Ingredient (per spray)

oxymetazoline hydrochloride 0.05%

Purpose

Nasal decongestant

Uses

- temporarily relieves nasal congestion due to:
  ▪ a cold
  ▪ hay fever
  ▪ upper respiratory allergies
  ▪ helps clear nasal passages; shrinks swollen membranes
  ▪ temporarily restores freer breathing through the nose

Warnings

Ask a doctor before use if you have

- heart disease
- thyroid disease
- high blood pressure
- diabetes
- trouble urinating due to an enlarged prostate gland

When using this product

- do not exceed recommended dosage
- temporary discomfort such as burning, stinging, sneezing, or an increase in nasal discharge may occur
- do not use for more than 3 days. Use only as directed. Frequent or prolonged use may cause nasal congestion to recur or worsen.
- use of this container by more than one person may spread infection

Stop use and ask a doctor if

symptoms persist

If pregnant or breast-feeding,

ask a health professional before use.

Keep out of reach of children.

If swallowed, get medical help or contact a Poison Control Center (1-800-222-1222) right away.

Directions

- adults and children 6 to under 12 years of age (with adult supervision): 2 or 3 sprays in each nostril not more often than every 10 to 12 hours. Do not exceed 2 doses in any 24 hour period
- children under 6 years of age: ask a doctor

Squeeze and unscrew to remove the protective cap. Align rail grooves and prime pump by depressing it firmly several times (see illustration on side). Hold bottle with thumb at base and nozzle between first and second fingers. With head upright, insert nozzle into nostril. Depress pump two or three times, all the way down, and sniff deeply.

Other Information

- store between 20° – 25°C (68° – 77°F). Avoid excessive heat or freezing.
- keep carton for full drug facts

Inactive ingredients

benzalkonium chloride, edetate disodium, glycerin, polyethylene glycol, povidone, propylene glycol, sodium phosphate dibasic, sodium phosphate monobasic, water

Questions or comments?

1-800-344-7239

PRINCIPAL DISPLAY PANEL

Nōstrilla®
Oxymetazoline HCl Nasal Solution
NASAL DECONGESTANT
1/2 FL. OZ (15 mL)